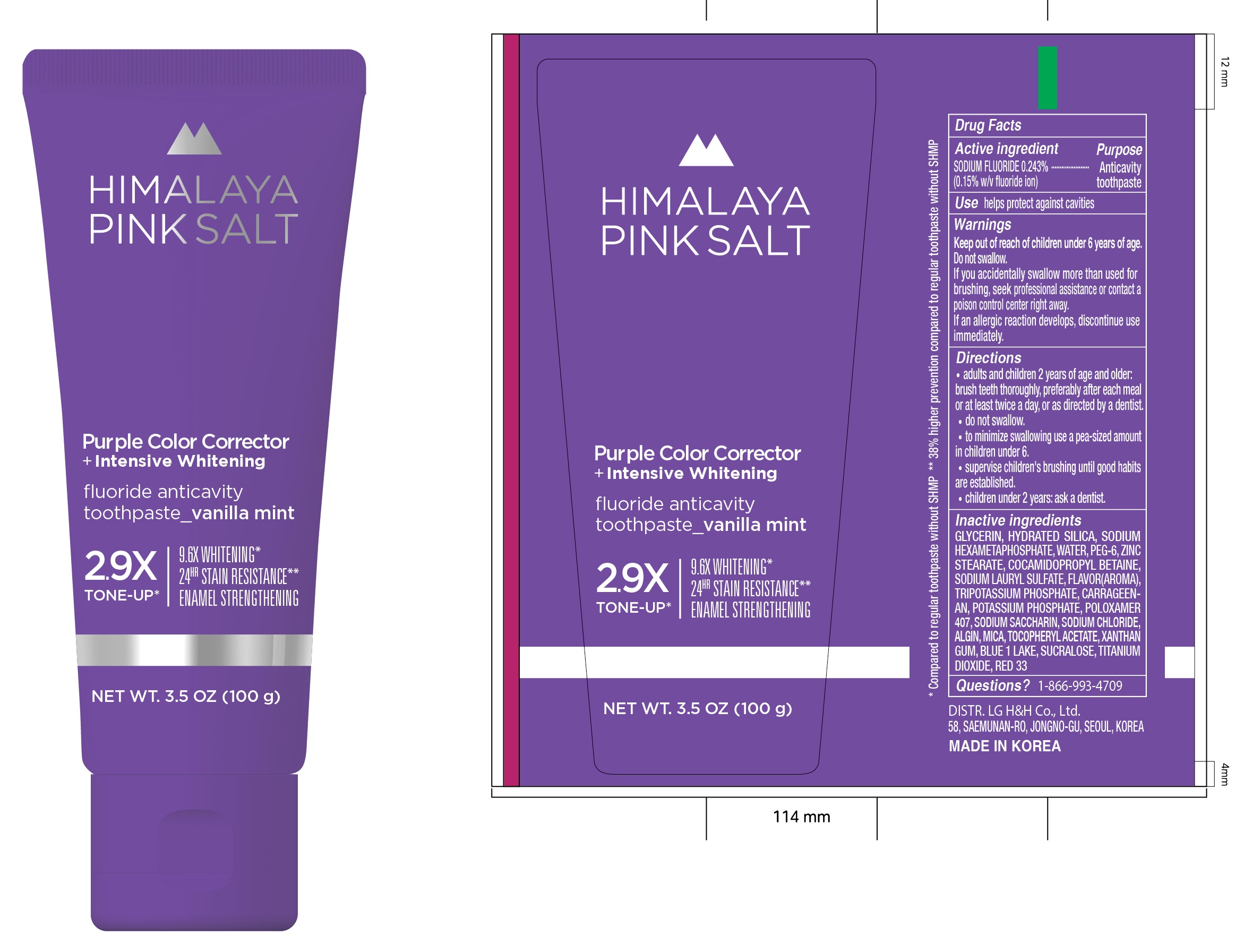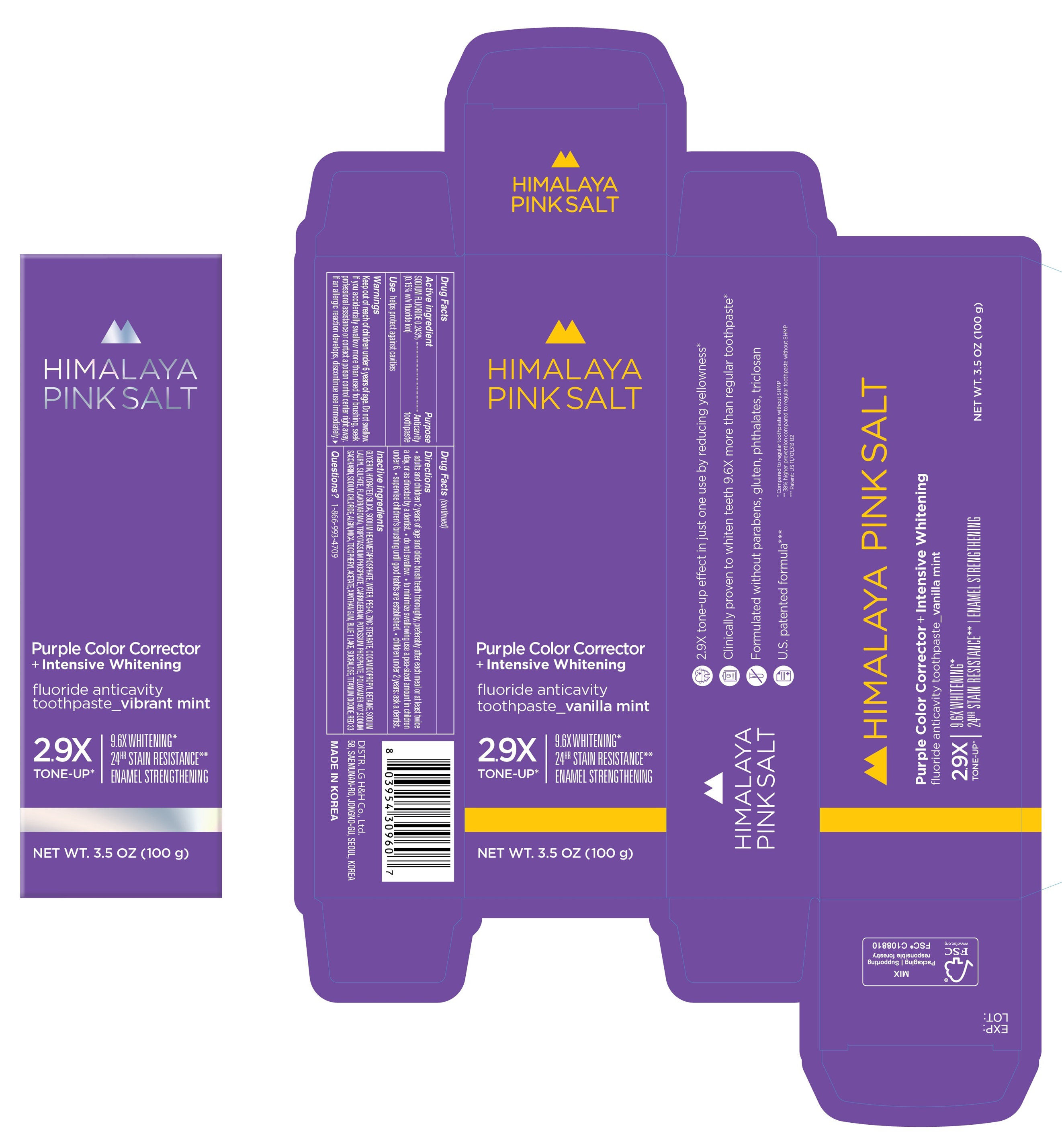 DRUG LABEL: HIMALAYA PINK SALT Purple Color Corrector plus Intensive Whitening Vanilla Mint
NDC: 43136-593 | Form: PASTE, DENTIFRICE
Manufacturer: Tai Guk Pharma. Co., Ltd.
Category: otc | Type: HUMAN OTC DRUG LABEL
Date: 20241101

ACTIVE INGREDIENTS: SODIUM FLUORIDE 1.5 mg/1 g
INACTIVE INGREDIENTS: POTASSIUM PHOSPHATE, TRIBASIC; GLYCERIN; COCAMIDOPROPYL BETAINE; WATER; SACCHARIN SODIUM; .ALPHA.-TOCOPHEROL ACETATE, DL-; FD&C BLUE NO. 1 ALUMINUM LAKE; SODIUM ALGINATE; SODIUM CHLORIDE; POLYETHYLENE GLYCOL 300; ZINC STEARATE; HYDRATED SILICA; SODIUM POLYMETAPHOSPHATE; SODIUM LAURYL SULFATE; CARRAGEENAN; MICA; D&C RED NO. 33; POTASSIUM PHOSPHATE, MONOBASIC; XANTHAN GUM; SUCRALOSE; POLOXAMER 407; TITANIUM DIOXIDE

HIMALAYA PINK SALT Purple Color Corrector + Intensive Whitening fluoride anticavity toothpaste_vanilla mint 100g

Active ingredient

SODIUM FLUORIDE 0.243%
(0.15% w/v fluoride ion)

Purpose

Anticavity
toopaste

Use

helps protect against cavities

Warnings

Keep out of reach of children under 6 years of age. Do not swallow.
If you accidentally swallow more than used for brushing, seek professional assistance or contact a poison control center right away.
If an allergic reaction develops, discontinue use immediately

Directions

- adults and children 2 years of age and and older: brush teeth thoroughly, preferably after each meal or at least twice a day, or as directed by a dentist.
- do not swallow.
- to minimize swallowing use a pea-sized amount in children under 6.
- supervise children's brushing until good habits are established.
- children under 2 years: ask a dentist.

Inactive ingredients

GLYCERIN, HYDRATED SILICA, SODIUM HEXAMETAPHOSPHATE, WATER, PEG-6, ZINC STEARATE, COCAMIDOPROPYL BETAINE, SODIUM LAURYL SULFATE, FLAVOR(AROMA), TRIPOTASSIUM PHOSPHATE, CARRAGEENAN, POTASSIUM PHOSPHATE, POLOXAMER 407, SODIUM SACCHARIN, SODIUM CHLORIDE, ALGIN, MICA, TOCOPHERYL ACETATE, XANTHAN GUM, BLUE 1 LAKE, SUCRALOSE, TITANIUM DIOXIDE, RED 33

Questions?

1-866-993-4709

DISTR. LG H&H Co., Ltd.
58, SAEMUNAN-RO, JONGNO-GU, SEOUL, KOREA
MADE IN KOREA

- 2.9X tone-up effect in just one use by reducing yellowness*
- Clinically proven to whiten teeth 9.6X more than regular toothpaste*
- Formulated without parabens, gluten, phthalates, triclosan
- U.S. patented formula***

* Compared to regular toothpaste without SHMP
** 38% higher prevention compared to regular toothpaste without SHMP
*** Patent : US 11,701, 313 B2

Principal Display Panel:

HIMALAYA
PINK SALT
Purple Color Corrector
+ Intensive Whitening
fluoride anticavity
toothpaste_ vanilla mint
2.9X
TONE-UP*
9.6X WHITENING*
24HR STAIN RESISTANCE**
ENAMEL STRENGTHENING

NET WT. 3.5 OZ (100 g)